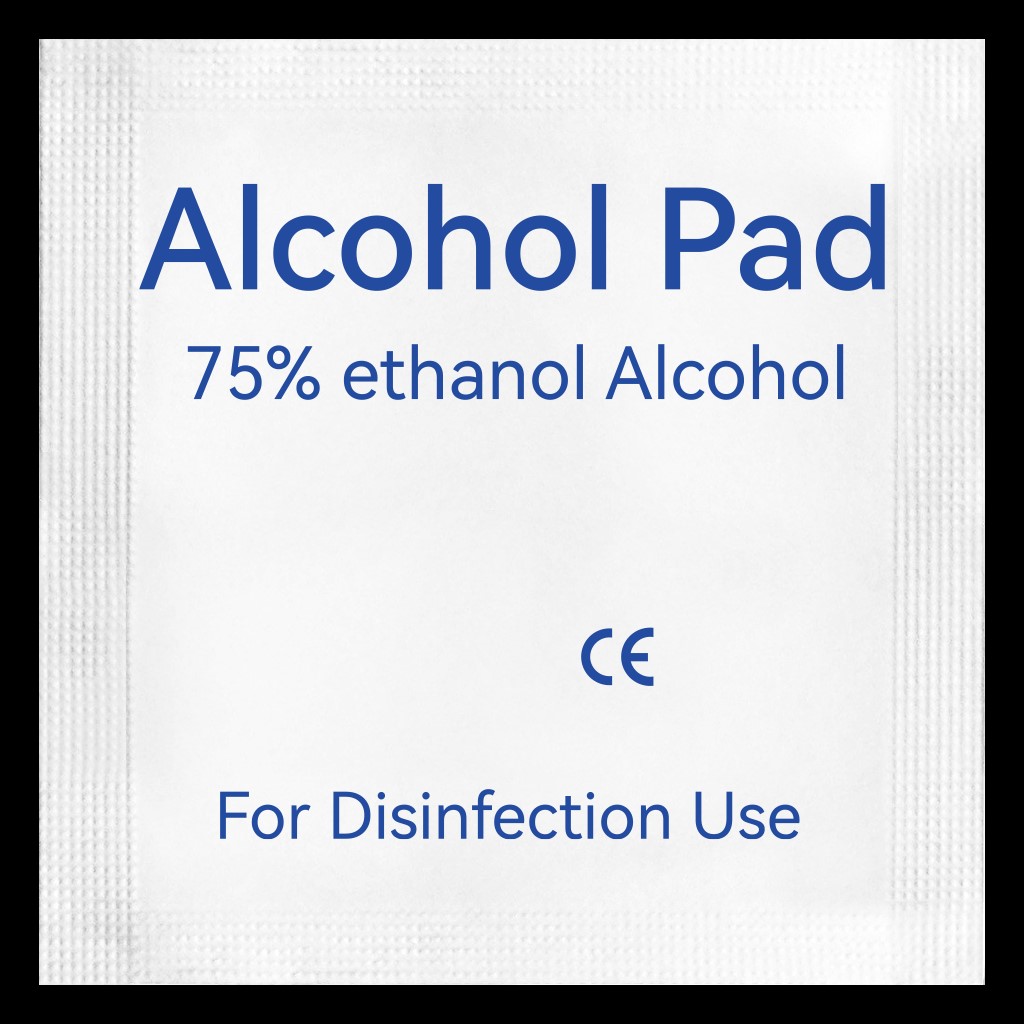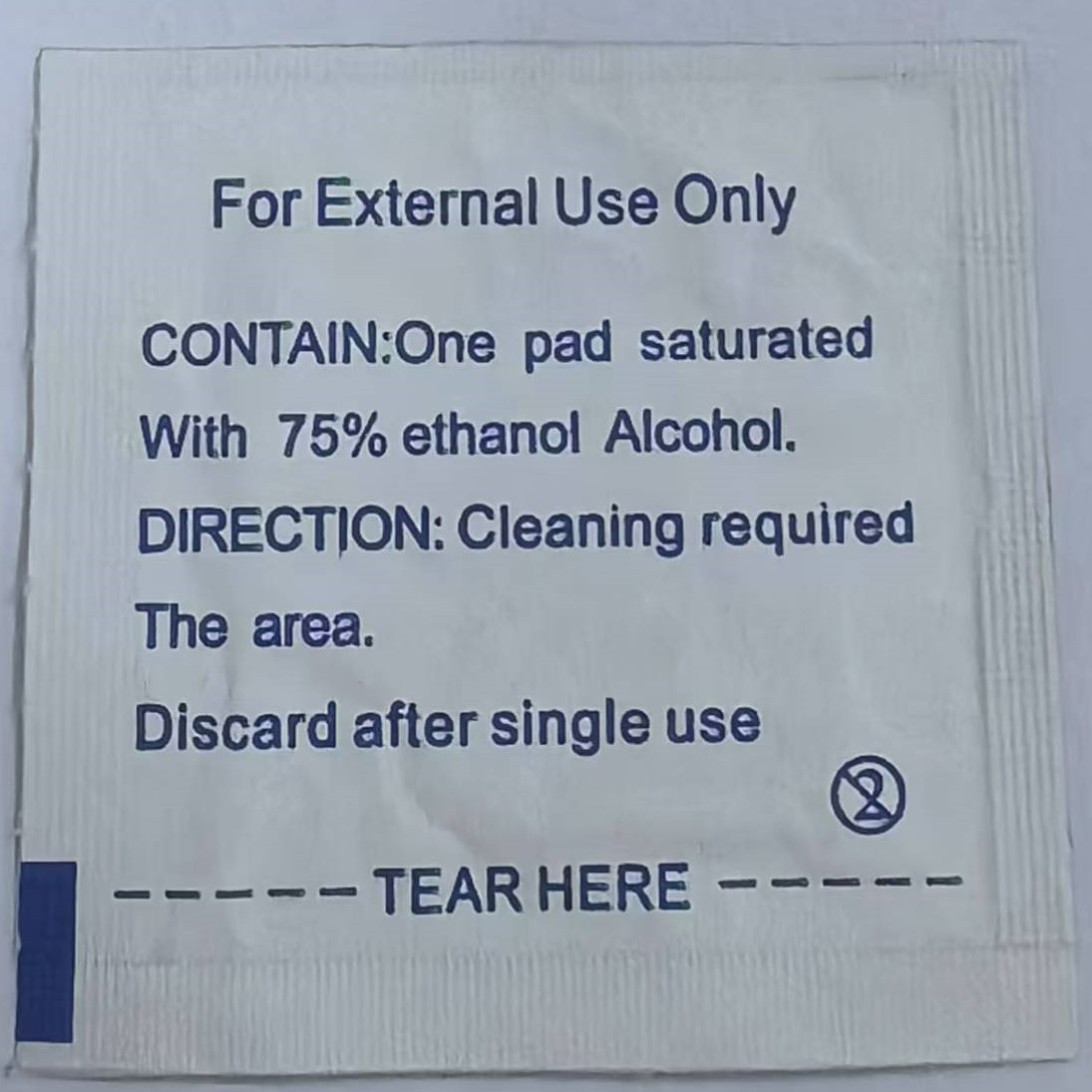 DRUG LABEL: Alcohol Pad
NDC: 80139-102 | Form: CLOTH
Manufacturer: Foshan Yiying Hygiene Products Co., Ltd.
Category: otc | Type: HUMAN OTC DRUG LABEL
Date: 20250110

ACTIVE INGREDIENTS: ALCOHOL 0.75 mL/1 mL
INACTIVE INGREDIENTS: WATER

75% Alcohol Pad

ACTIVE INGREDIENT

Ethanol, 75% v/v. Purpose: Disinfection

PURPOSE

Disinfection

INDICATIONS AND USAGE

For Disinfection Use

WARNINGS

For External Use Only

Single Use Only

Keep out of the reach of children

DOSAGE AND ADMINISTRATION

Cleaning required area.

Discard after single use

INACTIVE INGREDIENT

Water